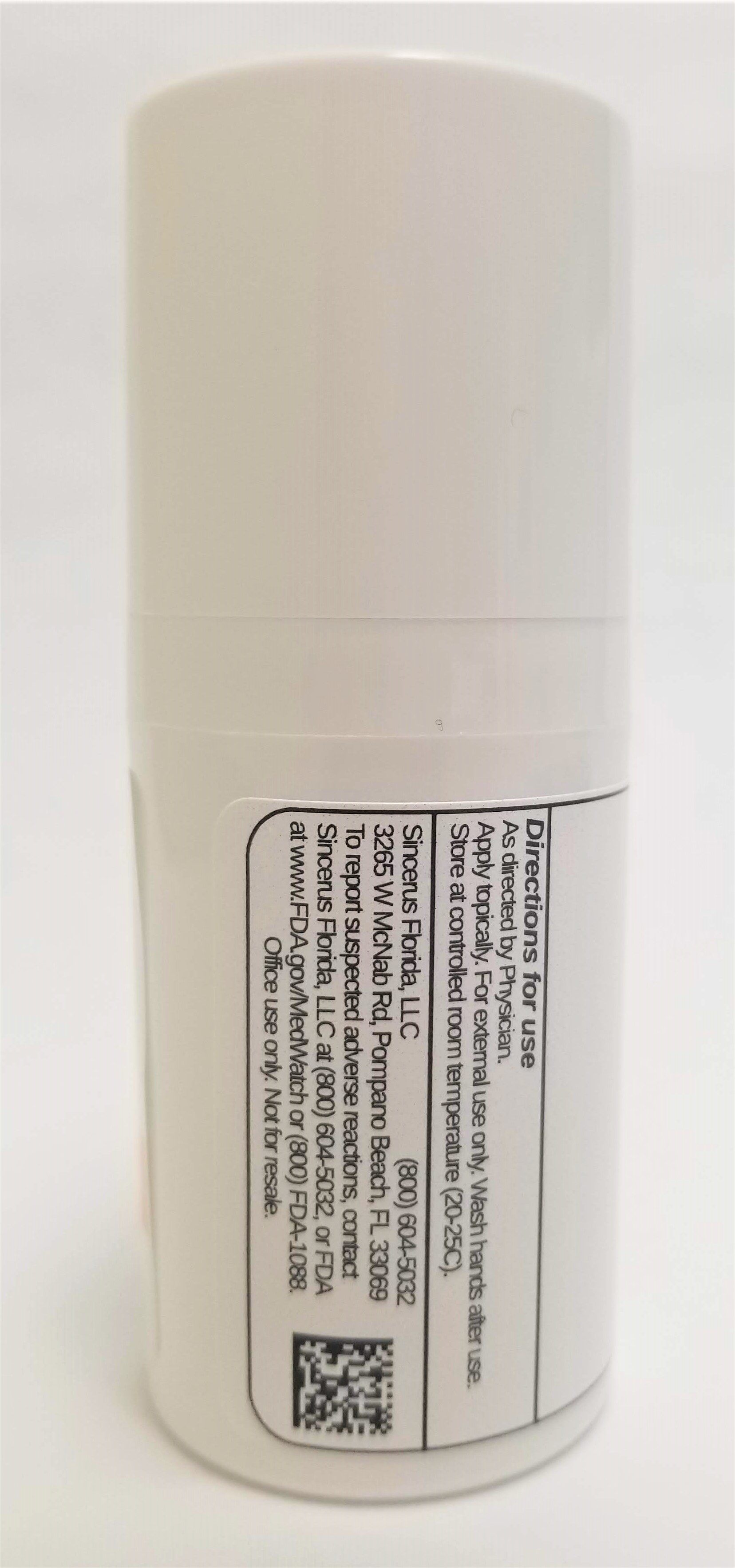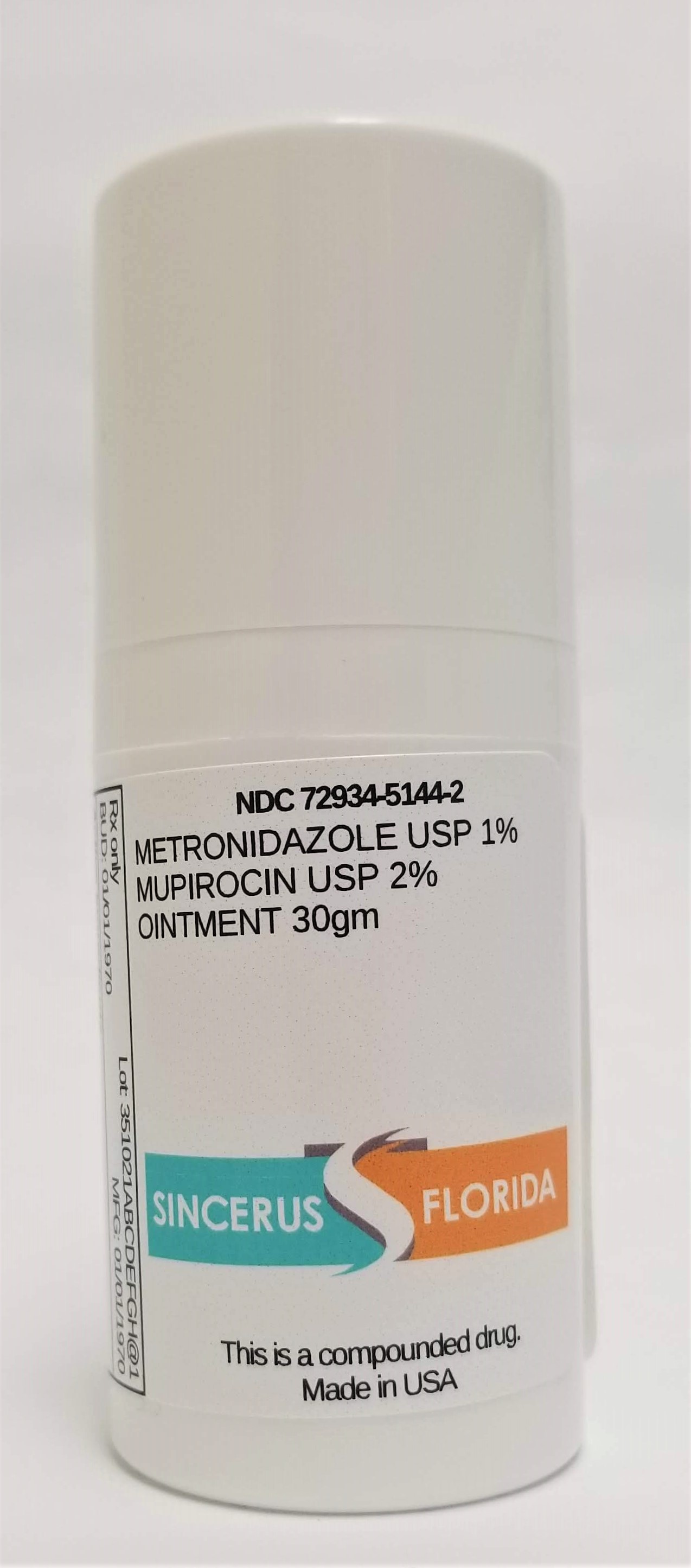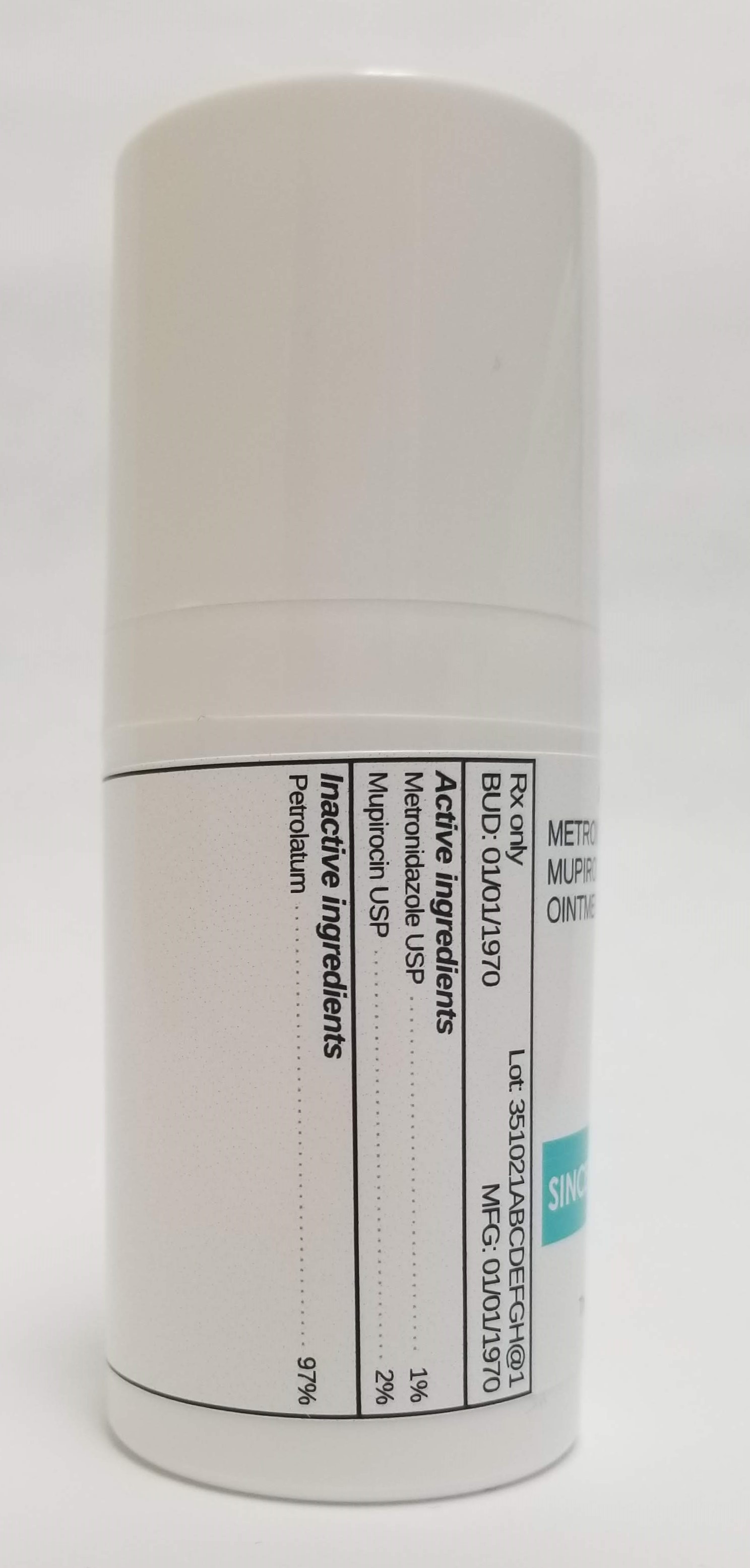 DRUG LABEL: METRONIDAZOLE 1% / MUPIROCIN 2%
NDC: 72934-5144 | Form: OINTMENT
Manufacturer: Sincerus Florida, LLC
Category: prescription | Type: HUMAN PRESCRIPTION DRUG LABEL
Date: 20190514

ACTIVE INGREDIENTS: METRONIDAZOLE 1 g/100 g; MUPIROCIN 2 g/100 g

METRONIDAZOLE 1% / MUPIROCIN 2%